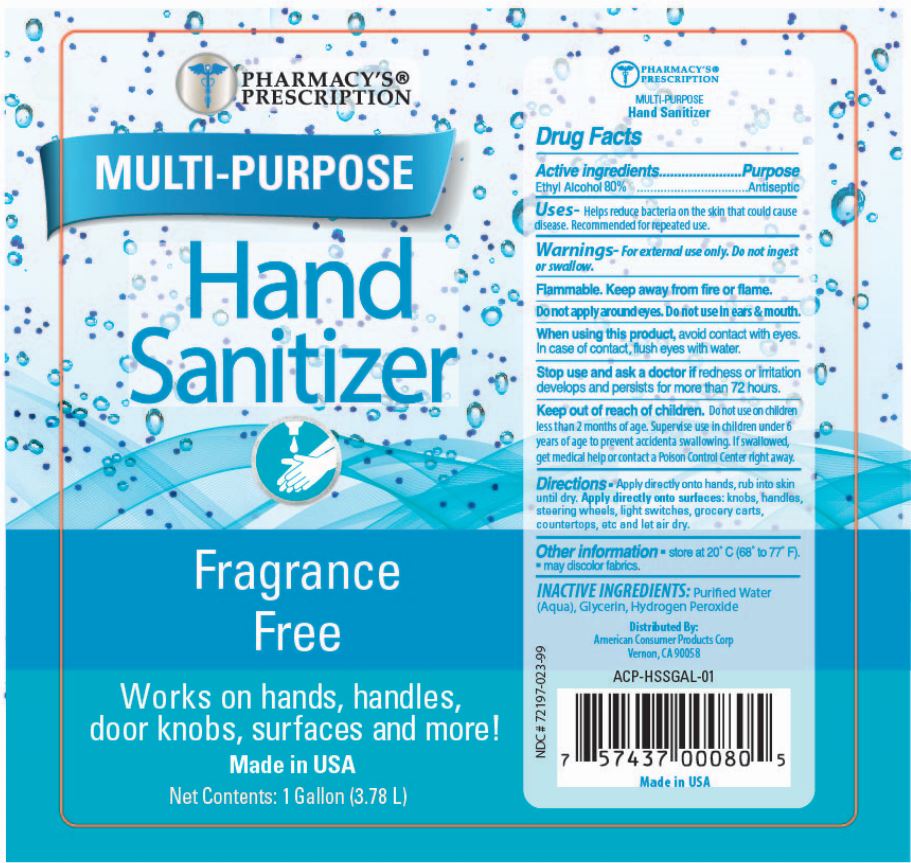 DRUG LABEL: Pharmacys Prescription Hand Sanitizer
NDC: 72197-023 | Form: SPRAY
Manufacturer: American Consumer Products Corp
Category: otc | Type: HUMAN OTC DRUG LABEL
Date: 20200428

ACTIVE INGREDIENTS: ALCOHOL 80 mL/100 mL
INACTIVE INGREDIENTS: WATER; GLYCERIN; HYDROGEN PEROXIDE

Pharmacys Prescription Hand Sanitizer

Active Ingredients

Active ingredients - Ethyl Alcohol 80%

Purpose

Purpose - Antiseptic

Warnings

Warnings - For external use only. Do not ingest or swallow.

Flammable. Keep away from fire or flame.

Do not apply around eyes. Do not use in ears & mouth.

Indications & Usage

When using this product, avoid contact with eyes. In case of contact, flush eyes with water.

Stop Use

Stop use and ask a doctor if redness or irritation develops and persists for more than 72 hours.

Keep out of reach of children. Do not use on children less than 2 months of age. Supervise use in children under 6 years of age to prevent accidental swallowing. If swallowed, get medical help or contact a Poison Control Center right away.

Directions

Directions - Apply directly onto hands, rub into skin until dry. Apply directly onto surfaces: knobs, handles, steering wheels, light swithches, grocery carts, countertops, etc and let air dry.

Other Information

Other information - store at 20° C (68° to 77° F).

-may discolor fabrics.

Inactive Ingredients

INACTIVE INGREDIENTS: Purified Water (Aqua), Glycerin, Hydrogen Peroxide

Distributed By:

American Consumer Products Corp

Vernon, CA 90058